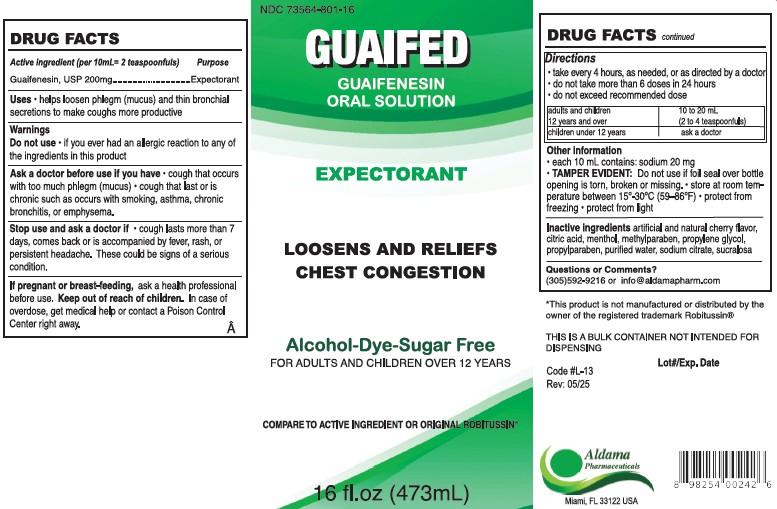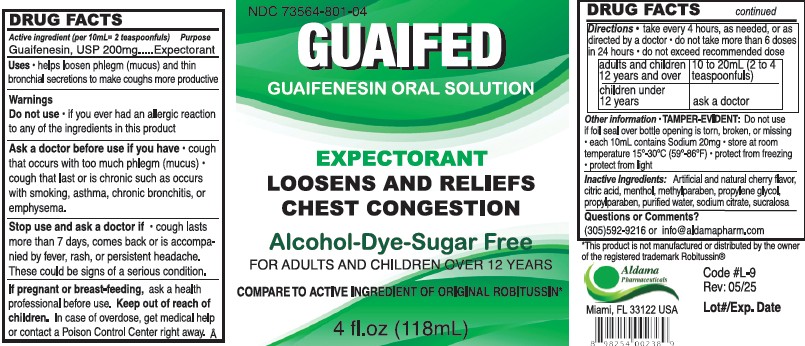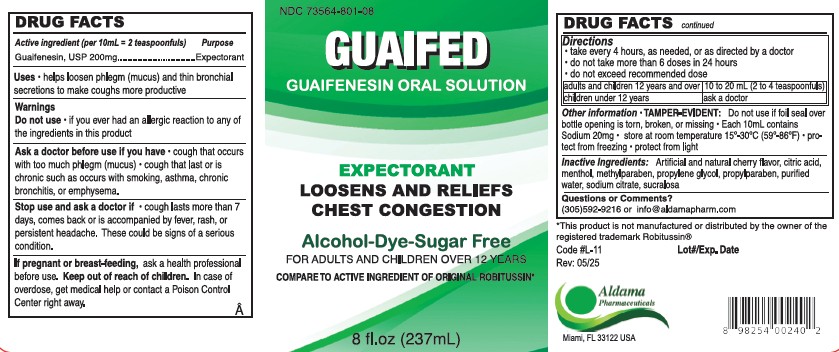 DRUG LABEL: Guaifed
NDC: 73564-801 | Form: LIQUID
Manufacturer: Aldama Pharmaceuticals, Inc
Category: otc | Type: HUMAN OTC DRUG LABEL
Date: 20251014

ACTIVE INGREDIENTS: GUAIFENESIN 200 mg/10 mL
INACTIVE INGREDIENTS: SUCRALOSE; MENTHOL; METHYLPARABEN; PROPYLENE GLYCOL; WATER; SODIUM CITRATE; CITRIC ACID

Guaifed

Active Ingredients:(per 10ml= 2 teaspoonfuls) Purpose

Guaifenesin 200 mg ................................................................... Expectorant

Purpose

Expectorant

Uses:

- Helps loosen phlegm (mucus) and thin bronchial secretions to make coughs more productive.

Warnings

- Do not use: if you ever had an allergic reaction to any of the ingredients in this product

Ask a doctor before use if you have

- cough that occurs with too much phlegm (mucus)
- cough that last or is chronic such as occurs with smoking, asthma, chronic bronchitis, or emphysema

Stop use and ask a doctor if

- cough lasts more than 7 days, comes back or is accompanied by fever, rash, or persistent headache. These could be signs of a serious condition.

PREGNANCY OR BREAST FEEDING

If pregnant or breast-feeding,ask a health professional before use.

Keep out of reach of children.

In case of overdose, get medical help or contact a Poison Control Center right away.

Directions

- take every 4 hours as needed, or as directed by doctor
- do not take more than 6 doses in 24 hours
- do not exceed recommended dose

Age | Dose
adults and children 12 years and over | 10 mL to 20 mL (2 to 4 teaspoonfuls)
children under 12 years of age | ask a doctor

Other information
• TAMPER - EVIDENT FEATURE: Do not use if foil seal over bottle opening is torn, broken or missing.
• each 10 mL contains: Sodium 20 mg
• store at room temperature 15° - 30°C (59° - 86°F).
• Protect from freezing
• Protect from light

Inactive Ingredients:

Artificial and natural cherry flavor, citric acid, menthol, Methylparaben, Propylene glycol, Propylparaben, purified water, sodium citrate, sucralose

Questions or Comments?305-592-9216 or info@aldamapharm.com